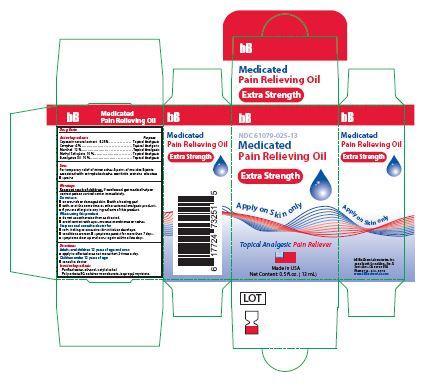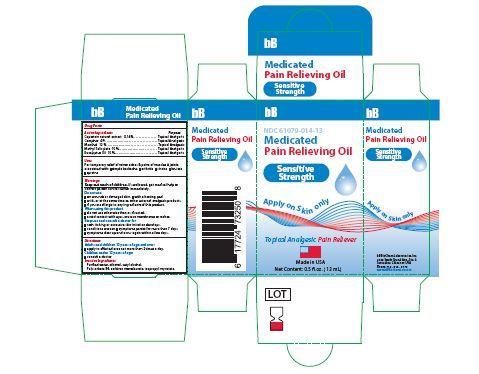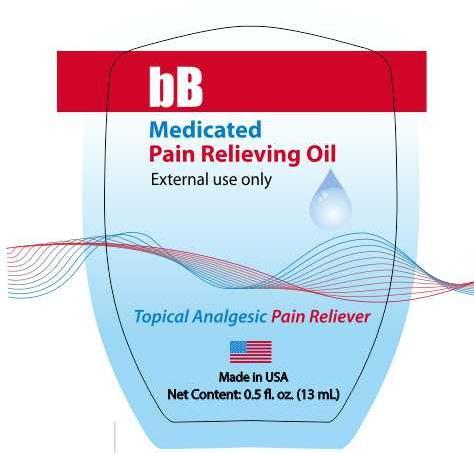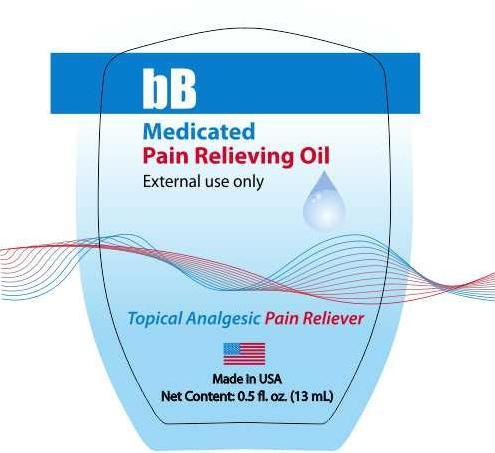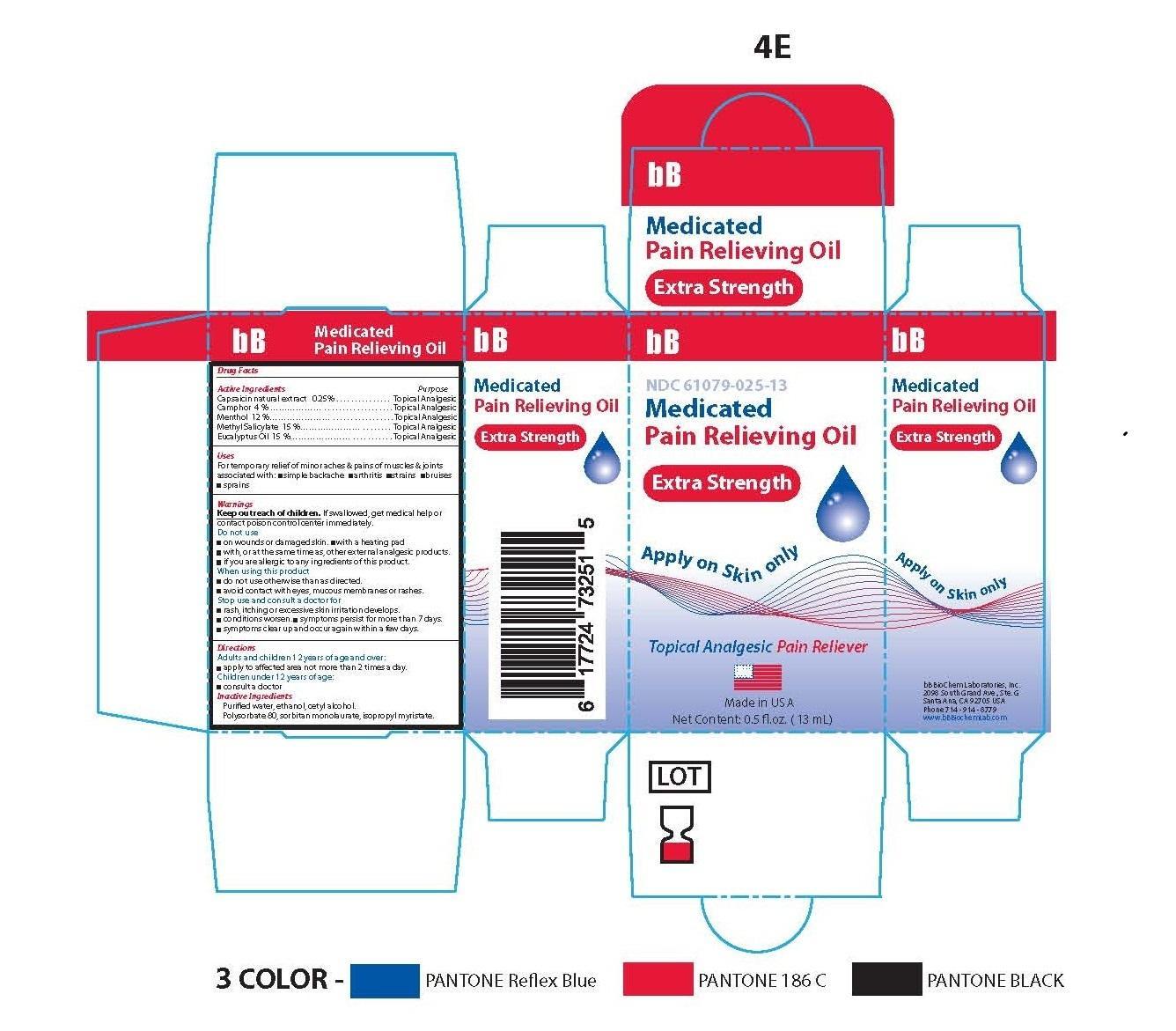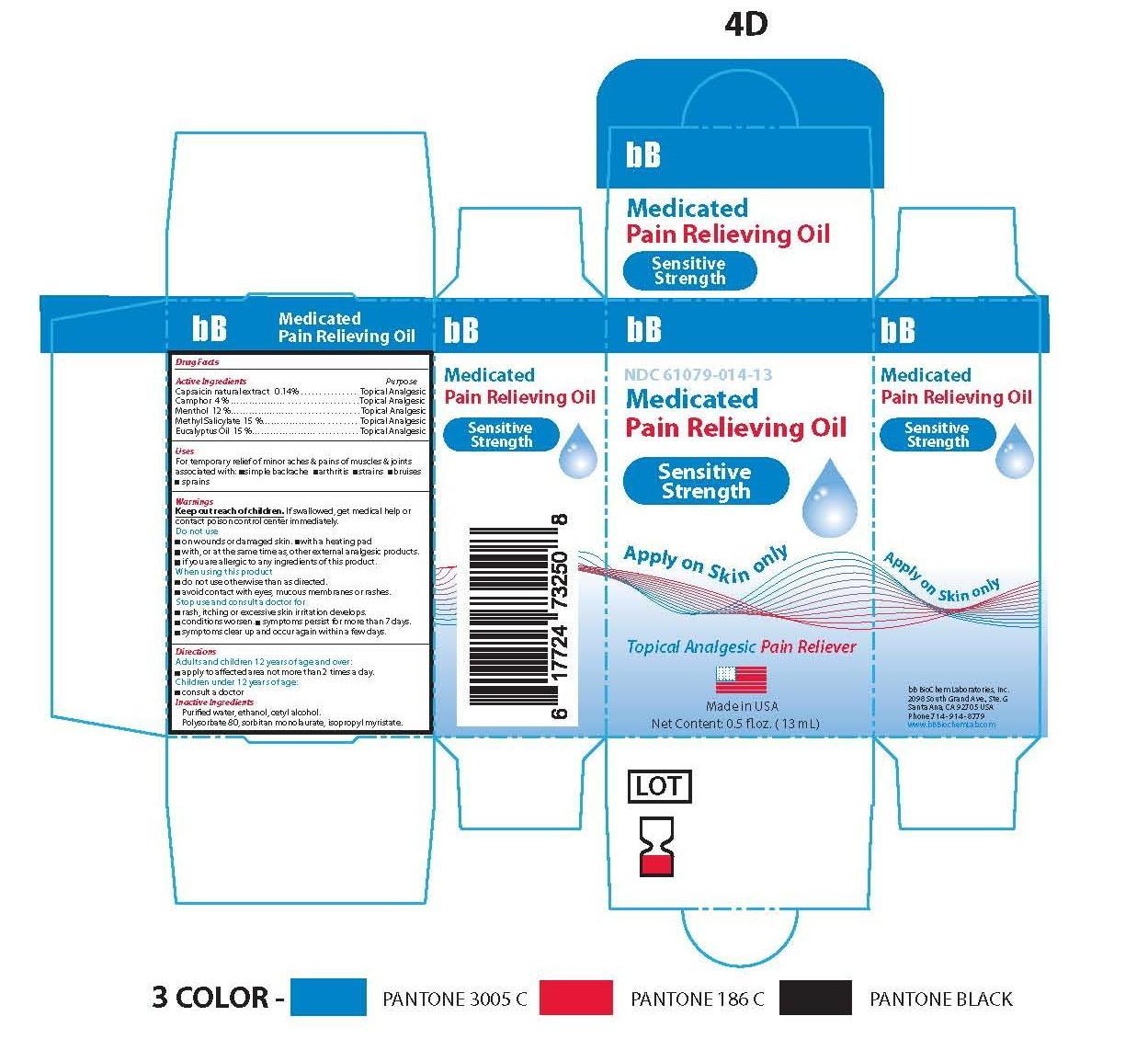 DRUG LABEL: bB Medicated Pain Relieving Oil
NDC: 61079-025 | Form: OIL
Manufacturer: BB BIOCHEM LABORATORIES, INC.
Category: otc | Type: HUMAN OTC DRUG LABEL
Date: 20141101

ACTIVE INGREDIENTS: CAMPHOR (SYNTHETIC) 3 g/100 g; LEVOMENTHOL 12 g/100 g; METHYL SALICYLATE 15 g/100 g; EUCALYPTUS OIL 15 g/100 g; CAPSAICIN .25 g/100 g
INACTIVE INGREDIENTS: CETYL ALCOHOL 3 g/100 g; POLYSORBATE 80 11 g/100 g; SORBITAN MONOLAURATE 7 g/100 g; ISOPROPYL MYRISTATE 27 g/100 g; ALCOHOL 3 g/100 g; WATER 4 g/100 g

bB MEDICATED PAIN RELIEVING OIL
APPLY ON SKIN ONLY

Active Ingredients

Capsaicin natural extract 0.25 % as capsaicin

Camphor 3 %

Menthol 12 %

Methyl Salicylate 15 %

Eucalyptus Oil 15 %

Purpose

Capsaicin natural extract ........................................... .Topical Analgesic

Camphor …………………………………………….........Topical Analgesic

Menthol ....................................................................... Topical Analgesic

Methyl Salicylate ..........................................................Topical Analgesic

Eucalyptus Oil ..............................................................Topical Analgesic

Uses

Apply on Skin only; for temporary relief of minor aches & pains of muscles & joints associated with sports and/or aging symptoms:

■ Simple backache ■ arthritis ■ strains ■ bruises ■ sprains

Warnings

Keep out reach of children

If swallowed, get medical help or contact poison control center immediately.

Do not use

■ on wounds or damaged skin.

■ with a heating pad

■ with, or at the same time as, other external analgesic products.

■ if you are allergic to any ingredients of this product.

When using this product:

■ do not use otherwise than as directed.

■ avoid contact with eyes, mucous membranes or rashes.

Stop use and consult a doctor for:

■ rash, itching or excessive skin irritation develops.

■ conditions worsen.

■ symptoms persist for more than7 days.

■ symptoms clear up and occur again within a few days.

If swallowed, get medical help or contact poison control center immediately.

Directions and Allergy alert:

If prone to allergic reaction from aspirin or salicylates, consult a doctor before use

Adults and children12 years of age and over:

■ clean and dry affected area.

■ apply to affected area not more than 2 times a day.

Children under 12 years of age:

■ consult a doctor

Flammable and Safe Handling

- keep away from fire or flame
- do not use where ignition sparks happens
- do not use in a confined space
- do not incinerate or heat the bottle
- do not expose bottle to temeprature exceeding 120 degree F (48 degree C)

Do NOT use:

- on wounds or damaged skins.
- with a heating pad.
- if you are allergic to any ingredients of this product

When using this product:

- do not use otherwise than directed to.
- avoid contact with the eyes, mucous membranes or rashes.
- do not bandage tightly.
- do not use on open wounds

Stop use and ask a doctor if any of the following happens:

- rash, itching or excessive skin irritation develops
- conditions worsen
- symptoms persist for more than 7 days
- symptoms clear up and return again within a few days

Pregancy or Breast Feeding.

If you are pregnant or breastfeeding, consult with your physician or a healthcare provider before use.

Keep out of reach of children.

Warnings

If swallowed, get medical help or contact poison control center immediately.

Children under 12 years of age:

■ consult a doctor

Inactive Ingredients

Purified water, Ethanol, Cetyl alcohol, Polysorbate 80, Sorbitan monolaurate, Isopropyl myristate.

Other Information

■ Due to its unique formulation, the solution can turn into different levels of white translucent, milky cloudiness at warmer temperatures; This is totally normal. Upon returning to cooler temperatures it should regain its typical transparency state.

■ Avoid storing product in direct sunlight.

■ Protect product from excessive moisture.

Principle Display Panel-Extra Strength-Capsaicin 0.25/100

NDC#61079-025-13

bB Medicated Oil Pain Reliever

Extra Strength

0.5 FL. OZ. (13 mL)

bB BioChem Laboratories, Inc.

Distributed by

bB BioChem Laboratories, Inc.

Santa Ana, CA 92705

bB BioChemUSA.com

Directions

Adults and children12 years of age and over:

- clean and dry affected area.
- apply to affected area not more than 2 times a day.

Children under 12 years of age:

- consult a doctor

Principle Display Panel-Sensitive Strength-Capsaicin 0.14/100

NDC#61079-014-13

bB Medicated Oil Pain Reliever

Sensitive Strength-Capsaicin 0.14/100

0.5 FL. OZ. (13 mL)

bB BioChem Laboratories, Inc.

Distributed by

bB BioChemLaboratories, Inc.

Santa Ana, CA 92705

bBBioChemUSA.com